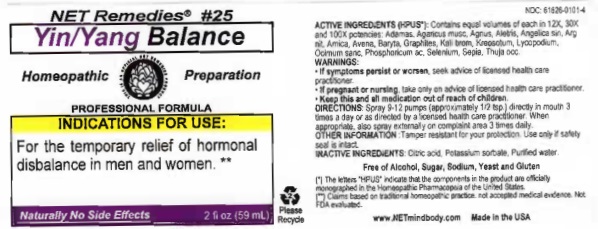 DRUG LABEL: Yin-Yang Balance
NDC: 61626-0101 | Form: LIQUID
Manufacturer: NET Remedies
Category: homeopathic | Type: HUMAN PRESCRIPTION DRUG LABEL
Date: 20210119

ACTIVE INGREDIENTS: DIAMOND 12 [hp_X]/59 mL; AMANITA MUSCARIA FRUITING BODY 12 [hp_X]/59 mL; CHASTE TREE 12 [hp_X]/59 mL; ALETRIS FARINOSA ROOT 12 [hp_X]/59 mL; ANGELICA SINENSIS ROOT 12 [hp_X]/59 mL; SILVER NITRATE 12 [hp_X]/59 mL; ARNICA MONTANA 12 [hp_X]/59 mL; AVENA SATIVA FLOWERING TOP 12 [hp_X]/59 mL; BARIUM IODIDE 12 [hp_X]/59 mL; GRAPHITE 12 [hp_X]/59 mL; POTASSIUM BROMIDE 12 [hp_X]/59 mL; WOOD CREOSOTE 12 [hp_X]/59 mL; LYCOPODIUM CLAVATUM SPORE 12 [hp_X]/59 mL; OCIMUM TENUIFLORUM TOP 12 [hp_X]/59 mL; PHOSPHORIC ACID 12 [hp_X]/59 mL; SELENIUM 12 [hp_X]/59 mL; SEPIA OFFICINALIS JUICE 12 [hp_X]/59 mL; THUJA OCCIDENTALIS LEAFY TWIG 12 [hp_X]/59 mL
INACTIVE INGREDIENTS: CITRIC ACID MONOHYDRATE; POTASSIUM SORBATE; WATER

ACTIVE INGREDIENT

ACTIVE INGREDIENTS (HPUS*): Contains equal volumes of each in 12X, 30X, and 100X potencies: Adamas, Agaricus musc, Agnus, Aletris, Angelica sin, Arg nit, Arnica, Avena, Baryta, Graphites, Kali brom, Keosotum, Lycopodium, Ocimum sanc, Phosphoricum ac, Selenium, Sepia, Thuja occ.

(*) The letters "HPUS" indicate that the components in the product are officially monographed in the Homeopathic Pharmacopeia of the United States,

(**) Claims based on traditional homeopathic practice, not accepted medical evidence. Not FDA evaluated.

INDICATIONS AND USAGE

INDICATIONS FOR USE: For the temporary relief of hormonal disbalance in men and women.**

WARNINGS

WARNINGS:• If symptoms persist or worsen, seek advice of licensed health care practitioner.
• If pregnant or nursing, take on only advice of licensed health care practitioner.

• Keep this and all medication out of reach of children.

KEEP OUT OF REACH OF CHILDREN

• Keep this and all medication out of reach of children.

DOSAGE AND ADMINISTRATION

DIRECTIONS: Spray 9-12 pumps (approximately 1/2 tsp.) directly in mouth 3 times a day or as directed by a licensed health care practitioner. When appropriate, also spray externally on complaint area 3 times daily.

OTHER INFORMATION: Tamper resistant for your protection. Use only if safety seal if intact.

INACTIVE INGREDIENTS: Citrid acid, Potassium sorbate, Purified water.

Free of Alcohol, Sugar, Sodium, Yeast and Gluten

QUESTIONS

www.NETmindbody.com

Made in the USA

PACKAGE LABEL

NET Remedies #25

Yin/Yang Balance

Homeopathic Preparation

PROFESSIONAL FORMULA

Naturally No Side Effects 2 fl oz (59 mL)

PURPOSE

INDICATIONS FOR USE: For the temporary relief of hormonal disbalance in men and women.**